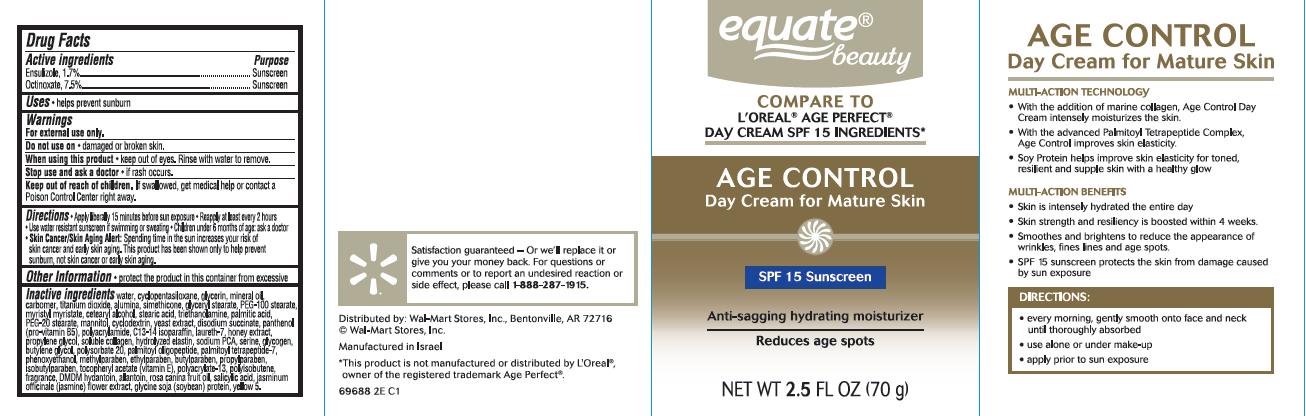 DRUG LABEL: Age Control Anti-Sagging and Ultra Hydrating Day SPF 15
NDC: 49035-688 | Form: CREAM
Manufacturer: Wal-Mart Stores, Inc.
Category: otc | Type: HUMAN OTC DRUG LABEL
Date: 20131022

ACTIVE INGREDIENTS: ENSULIZOLE 1.7 g/100 g; OCTINOXATE 7.5 g/100 g
INACTIVE INGREDIENTS: WATER; CYCLOMETHICONE 5; GLYCERIN; MINERAL OIL; CARBOMER COPOLYMER TYPE A (ALLYL PENTAERYTHRITOL CROSSLINKED); TITANIUM DIOXIDE; ALUMINUM OXIDE; DIMETHICONE; GLYCERYL MONOSTEARATE; PEG-100 STEARATE; MYRISTYL MYRISTATE; CETOSTEARYL ALCOHOL; STEARIC ACID; TROLAMINE; PALMITIC ACID; PEG-20 STEARATE; MANNITOL; ALFADEX; YEAST; SODIUM SUCCINATE ANHYDROUS; PANTHENOL; POLYACRYLAMIDE (10000 MW); C13-14 ISOPARAFFIN; LAURETH-7; HONEY; PROPYLENE GLYCOL; BOVINE TYPE I COLLAGEN; HYDROLYZED ELASTIN, BOVINE, ALKALINE (1000 MW); SODIUM PYRROLIDONE CARBOXYLATE; SERINE; GLYCOGEN; BUTYLENE GLYCOL; PALMITOYL OLIGOPEPTIDE; PALMITOYL TETRAPEPTIDE-7; PHENOXYETHANOL; METHYLPARABEN; ETHYLPARABEN; BUTYLPARABEN; PROPYLPARABEN; ISOBUTYLPARABEN; .ALPHA.-TOCOPHEROL ACETATE; POLYISOBUTYLENE (1000 MW); POLYSORBATE 20; DMDM HYDANTOIN; ALLANTOIN; ROSA CANINA FRUIT OIL; SALICYLIC ACID; JASMINUM OFFICINALE FLOWER; FD&C YELLOW NO. 5; SOY STEROL

equate® beauty Age Control Day Cream for Mature Skin

Active ingredient

Ensulizole 1.7%

Octinoxate 7.5%

Purpose

Sunscreen

Uses

- helps prevent sunburn

Warnings

For external use only.

Do not use on

- damaged or broken skin.

When using this product

- keep out of eyes. Rinse with water to remove.

Stop use and ask a doctor

- if rash occurs.

Keep Out of Reach of Children.

If swallowed, get medical help or contact a Poison Control Center right away.

Directions

- Apply liberally 15 minutes before sun exposure.
- Reapply at least every 2 hours
- Use a water resistant sunscreen if swimming or sweating
- Children under 6 months of age: ask a doctor
- Skin Cancer/Skin Aging Alert: Spending time in the sun increases your risk of skin cancer and early skin aging. This product has been shown only to help prevent sunburn, not skin cancer or early skin aging.

Other Information

- protect the product in this container from excessive heat and direct sun

Inactive Ingredients

water, cyclopentasiloxane, glycerin, mineral oil, carbomer, titanium dioxide, alumina, simethicone, glyceryl stearate, PEG-100 stearate, myristyl myristate, cetearyl alcohol, stearic acid, triethanolamine, palmitic acid, PEG-20 stearate, mannitol, cyclodextrin, yeast extract, disodium succinate, panthenol (vitamin B5), polyacrylamide, C13-14 isoparaffin, laureth-7, honey extract, propylene glycol, soluble collagen, hydrolyzed elastin, sodium PCA, serine, glycogen, butylene glycol, polysorbate 20, palmitoyl oligopeptide, palmitoyl tetrapeptide-7, phenoxyethanol, methylparaben, ethylparaben, butylparaben, propylparaben, isobutylparaben, tocopheryl acetate (vitamin E), polyacrylate-13, polyisobutene, fragrance, DMDM hydantoin, allantoin, rosa canina fruit oil, salicylic acid, jasminum officinale (jasmine) flower extract, glycine soja (soybean) protein, yellow 5.

Package/Label Principal Display Panel

equate® beauty AGE CONTROL Day Cream for Mature Skin

Compare to L'Oreal® Age Perfect®
Day Cream SPF 15 Ingredients*

SPF 15 Sunscreen

Anti-sagging hydrating moisturizer

Reduces age spots

NET WT 2.5 FL OZ (70 g)

Satisfaction guaranteed - Or we'll replace it or give you your money back. For questions or comments or to report an undesired reaction or side effect, please call 1-888-287-1915.

Distributed by:
Wal-Mart Stores, Inc.
Bentonville, AR 72716
©Wal-Mart Stores, Inc.
Manufactured in Israel

*This product is not manufactured or distributed by L'Oreal® , owner of the registered trademark Age Perfect®

69688 2E C1

Carton Label